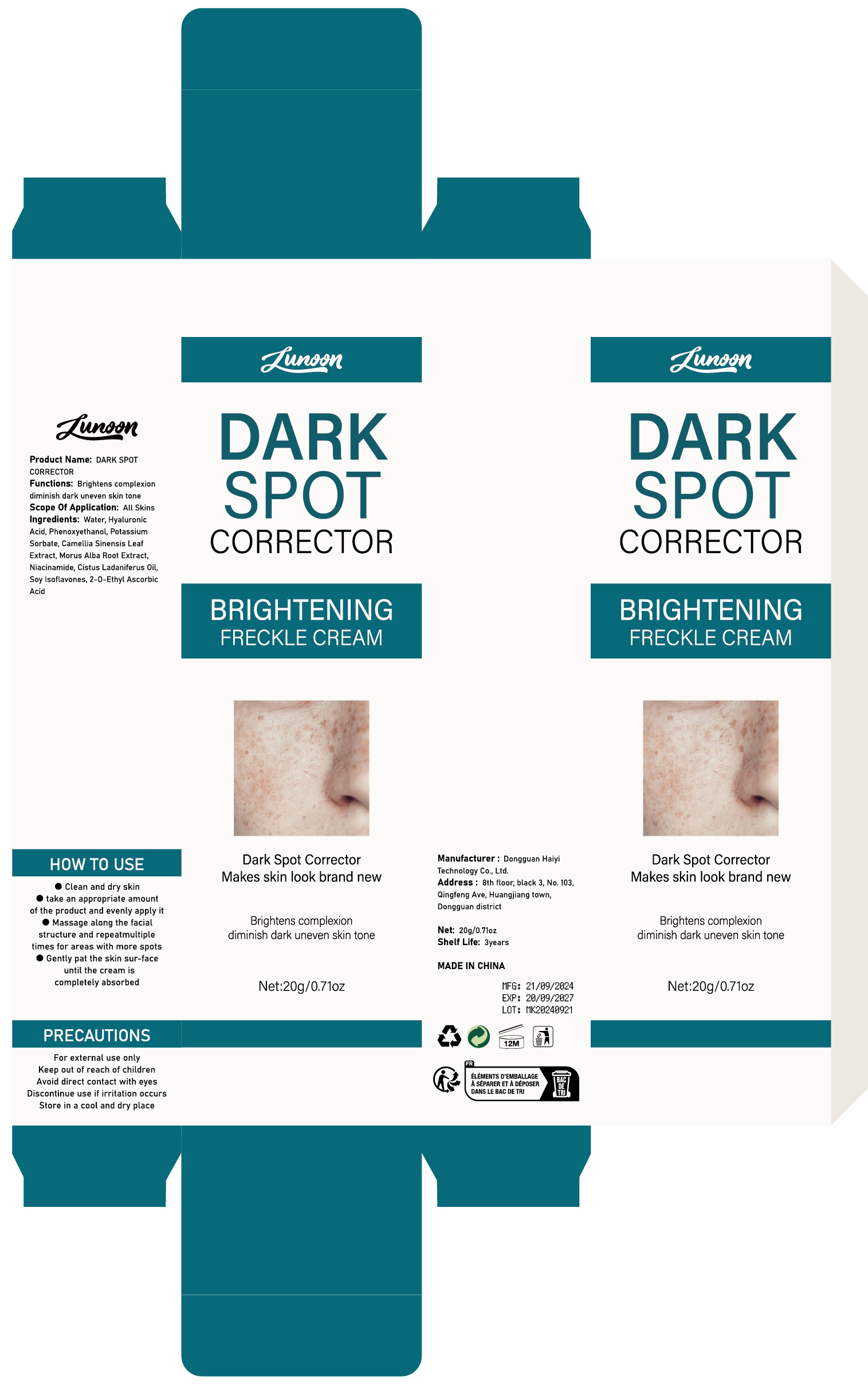 DRUG LABEL: DARK SPOT CORRECTOR
NDC: 84732-077 | Form: CREAM
Manufacturer: Dongguan Haiyi Technology Co.,Ltd.
Category: otc | Type: HUMAN OTC DRUG LABEL
Date: 20241031

ACTIVE INGREDIENTS: HYALURONIC ACID 1 mg/20 g
INACTIVE INGREDIENTS: MORUS ALBA ROOT; POTASSIUM SORBATE; GREEN TEA LEAF; NIACINAMIDE; 2-O-ETHYL ASCORBIC ACID; PHENOXYETHANOL; SOY ISOFLAVONES; WATER; CISTUS LADANIFERUS OIL

Active ingredient

Hyaluronic Acid

Inactive ingredient

Water, Phenoxyethanol, Potassium Sorbate, Camellia Sinensis Leaf Extract, Morus Alba Root Extract,Niacinamide, Cistus Ladaniferus Oil,Soy lsoflavones,2-0-Ethyl AscorbicAcid

Purpose section

Brightens complexion diminish dark uneven skin tone

Warning

For external use only

Keep out of reach of children

Avoid direct contact with eyes

Discontinue use if irritation occurs

Store in a cool and dry place

stop use

This product may cause allergic reactions in asmall number of people.
lf youexperience any discomfort,please stop using it immediately.

not use

Not suitable for use by children, pregnantor breast feeding people.

OUT OF CHILDREN

KEEP THE PRODUCT OUT OF REACH OF CHILDREN to

HOW TO USE

Clean and dry skin

take an appropriate amountof the product and evenly apply it

Massage along the facialstructure and repeatmultipletimes for areas with more spots

Gently pat the skin sur-faceuntil the cream iscompletely absorbed

Dosage

take an appropriateamount,Use 2-3 times a week